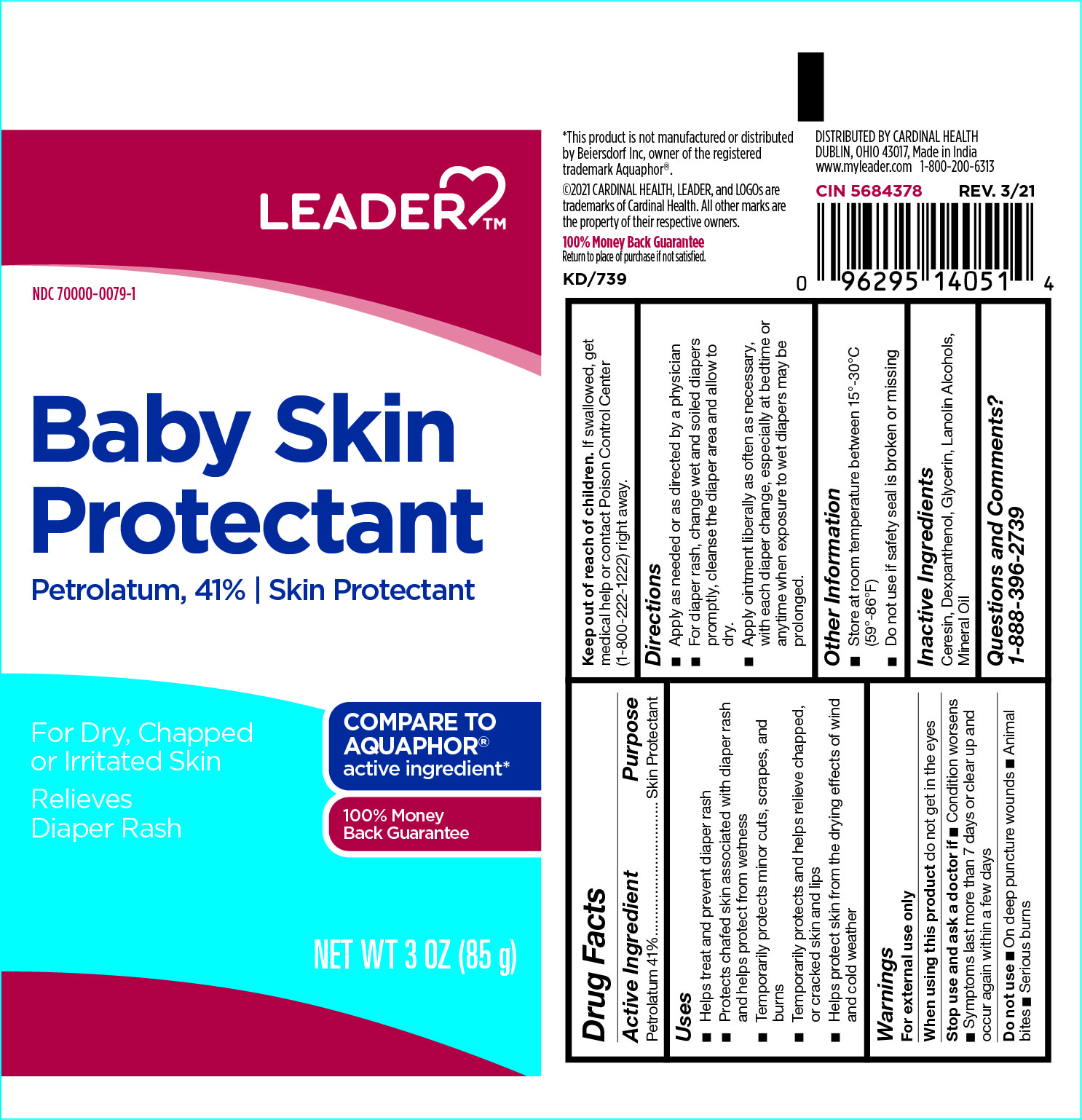 DRUG LABEL: Leader Baby Skin Protectant
NDC: 70000-0079 | Form: OINTMENT
Manufacturer: Cardinal Health
Category: otc | Type: HUMAN OTC DRUG LABEL
Date: 20251125

ACTIVE INGREDIENTS: PETROLATUM 41 g/100 g
INACTIVE INGREDIENTS: GLYCERIN; DEXPANTHENOL; LANOLIN ALCOHOLS; MINERAL OIL; CERESIN

Baby Skin Protectant

Active Ingredient

Petrolatum 41%

Purpose

Skin Protectant

Uses

- Helps treat and prevent diaper rash
- Protects chafed skin associated with diaper rash and helps protect from wetness
- Temporarily protects minor cuts, scrapes,and burns
- Temporarily protects and helps relieve chapped, or cracked skin and lips
- Helps protect skin from the drying effects of wind and cold weather

Warnings

For external use only

When using this product

do not get in the eyes

Stop us and ask a doctor if

- Condition worsens
- Symptoms last more than 7 days or clear up and occur again within a few days

Do not use

- On deep puncture wounds
- Animal bites
- Serious burns

Keep out of reach of children.

If swallowed, get medical help or contact Poison Control Center (1-800-222-1222) right away.

Directions

- Apply as needed or as directed by a physician
- For diaper rash, change wet and soiled diapers promptly, cleanse the diaper area and allow to dry.
- Apply ointment liberally as often as necessary, with each diaper change, especially at bedtime or anytime when exposure to wet diapers may be prolonged.

Other Information

- Store at room temperature between 15º-30°C (59°-86°F)
- Do not use if safety seal is broken or missing

Inactive Ingredients

Ceresin, Dexpanthenol, Glycerin, Lanolin Alcohols, Mineral Oil

Questions and Comments?

1-888-396-2739